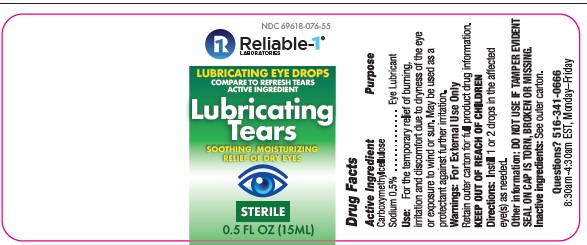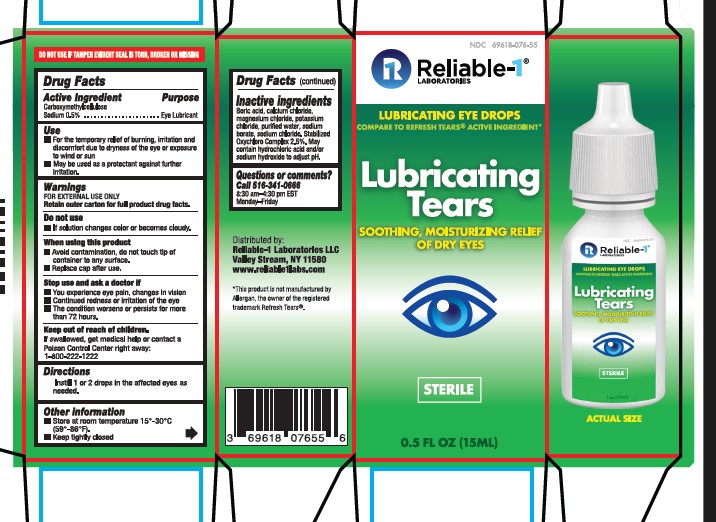 DRUG LABEL: Lubricating Tears
NDC: 69618-076 | Form: SOLUTION/ DROPS
Manufacturer: Reliable 1 Laboritories LLC
Category: otc | Type: HUMAN OTC DRUG LABEL
Date: 20250115

ACTIVE INGREDIENTS: CARBOXYMETHYLCELLULOSE SODIUM, UNSPECIFIED FORM 5 mg/1 mL
INACTIVE INGREDIENTS: BORIC ACID; SODIUM CHLORIDE; CALCIUM CHLORIDE; SODIUM HYDROXIDE; SODIUM CHLORITE; MAGNESIUM CHLORIDE; SODIUM BORATE; POTASSIUM CHLORIDE; WATER; HYDROCHLORIC ACID

Lubricating Tears (CMC Drops)

Active Ingredient

Drug Facts

Carboxymethylcellulose sodium 0.5%

Purpose

Eye lubricant

USES

- For the temporary relief of burning, irritation, and discomfort due to dryness of the eye or exposure to wind or sun.
- May be used as a protectant against further irritation.

Warnings

- For external use only.
- Retain outer carton for full product drug facts

Do Not Use

- If solution changes color or becomes cloudy.

When using this product

- To avoid contamination, do not touch tip of container to any surface.
- Replace cap after using.

Stop use and ask a doctor if

- you experience eye pain, changes in vision
- continued redness or irritation of the eye
- if the condition worsens or persists for more than 72 hours.

Keep out of reach of children.

If swallowed, get medical help or contact a Poison Control Center right away. 1-800-222-1222

OTHER INFORMATION

Store at room temperature 15°-30°C (59°-86°F).
Keep tightly closed

Questions or comments?

1-516-341-0666

8:30AM – 4:30PM

Monday – Friday

Directions

Instill 1 or 2 drops in the affected eye(s) as needed.

INACTIVE INGREDIENT

Boric acid, calcium chloride, magnesium chloride, potassium chloride, purified water, sodium borate, sodium chloride. Stabilized Oxychloro Complex 2.5%. May contain hydrochloric acid and/or sodium hydroxide to adjust pH.

PRINCIPAL DISPLAY PANEL

Lubricating Tears

NDC 69618-076-55
Lubricant Eye Drops

Compare to Refresh Tears® active ingredient

Soothing, moisturizing relief of dry eyes
Sterile

0.5 fl oz (15 mL)